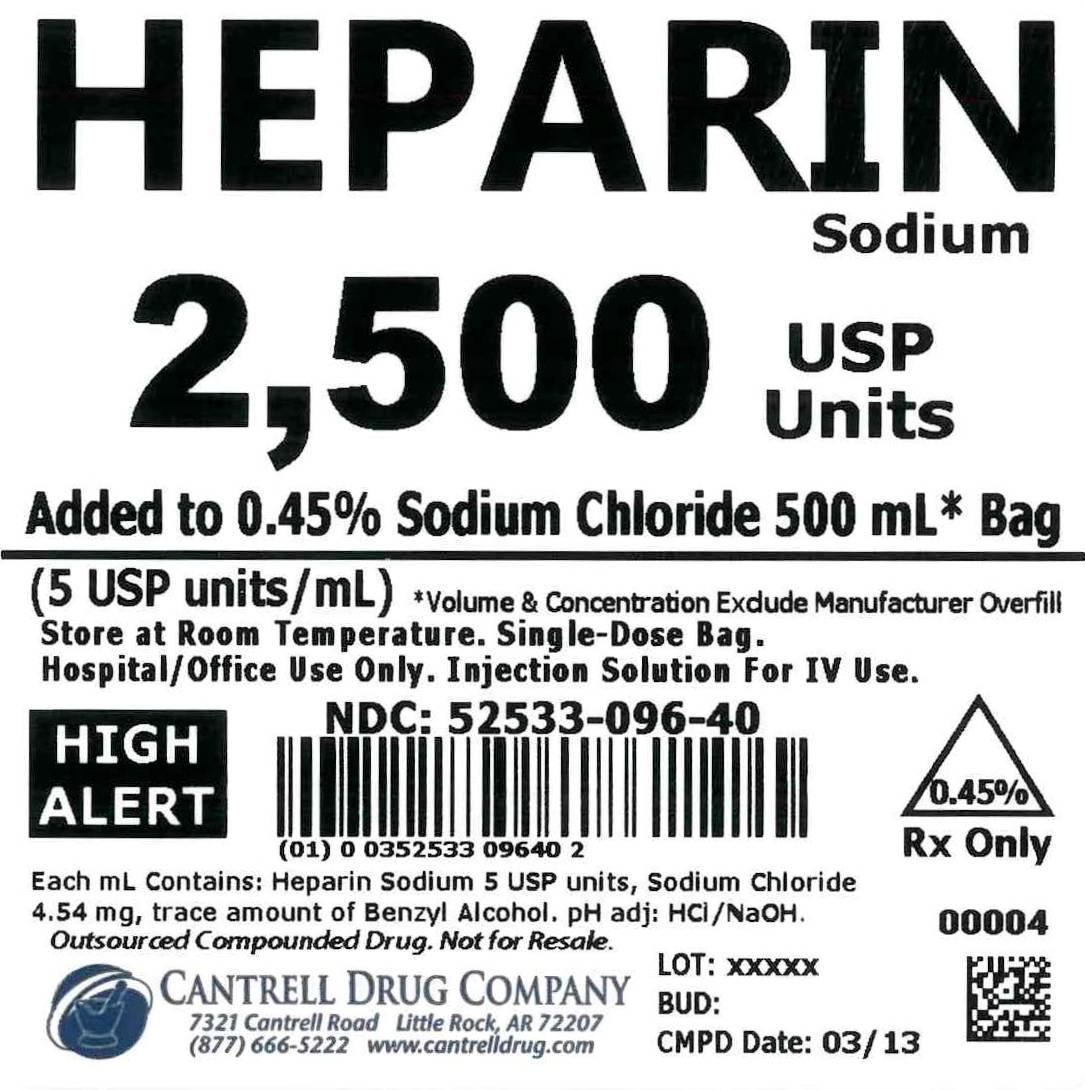 DRUG LABEL: Heparin Sodium
NDC: 52533-096 | Form: INJECTION, SOLUTION
Manufacturer: Cantrell Drug Company
Category: prescription | Type: HUMAN PRESCRIPTION DRUG LABEL
Date: 20141224

ACTIVE INGREDIENTS: Heparin Sodium 5 [USP'U]/1 mL
INACTIVE INGREDIENTS: SODIUM CHLORIDE 4.5 mg/1 mL; BENZYL ALCOHOL 0.00005 mL/1 mL; Water

Heparin Sodium 2,500 USP Units Added to 4.5% Sodium Chloride 500 mL Bag